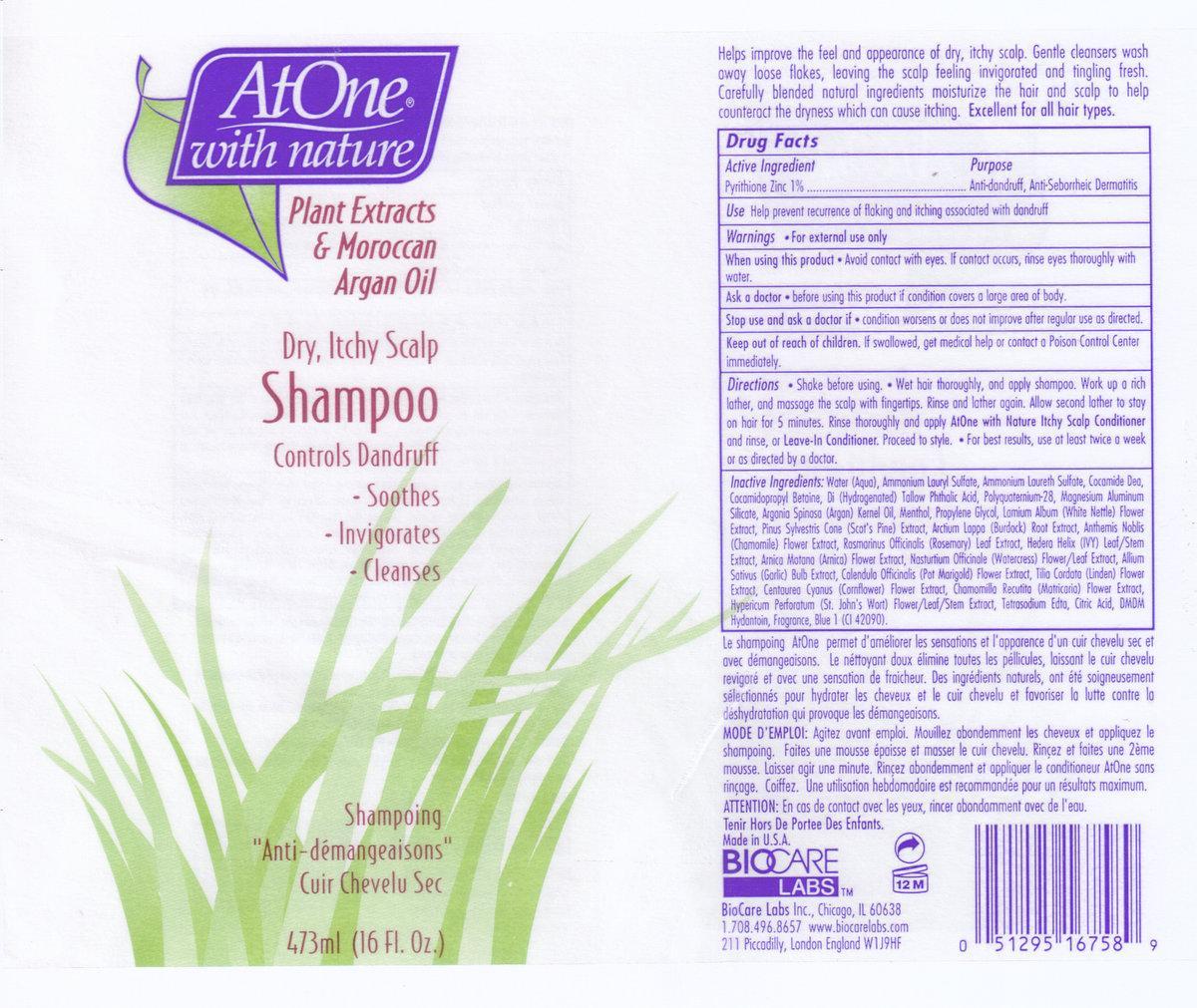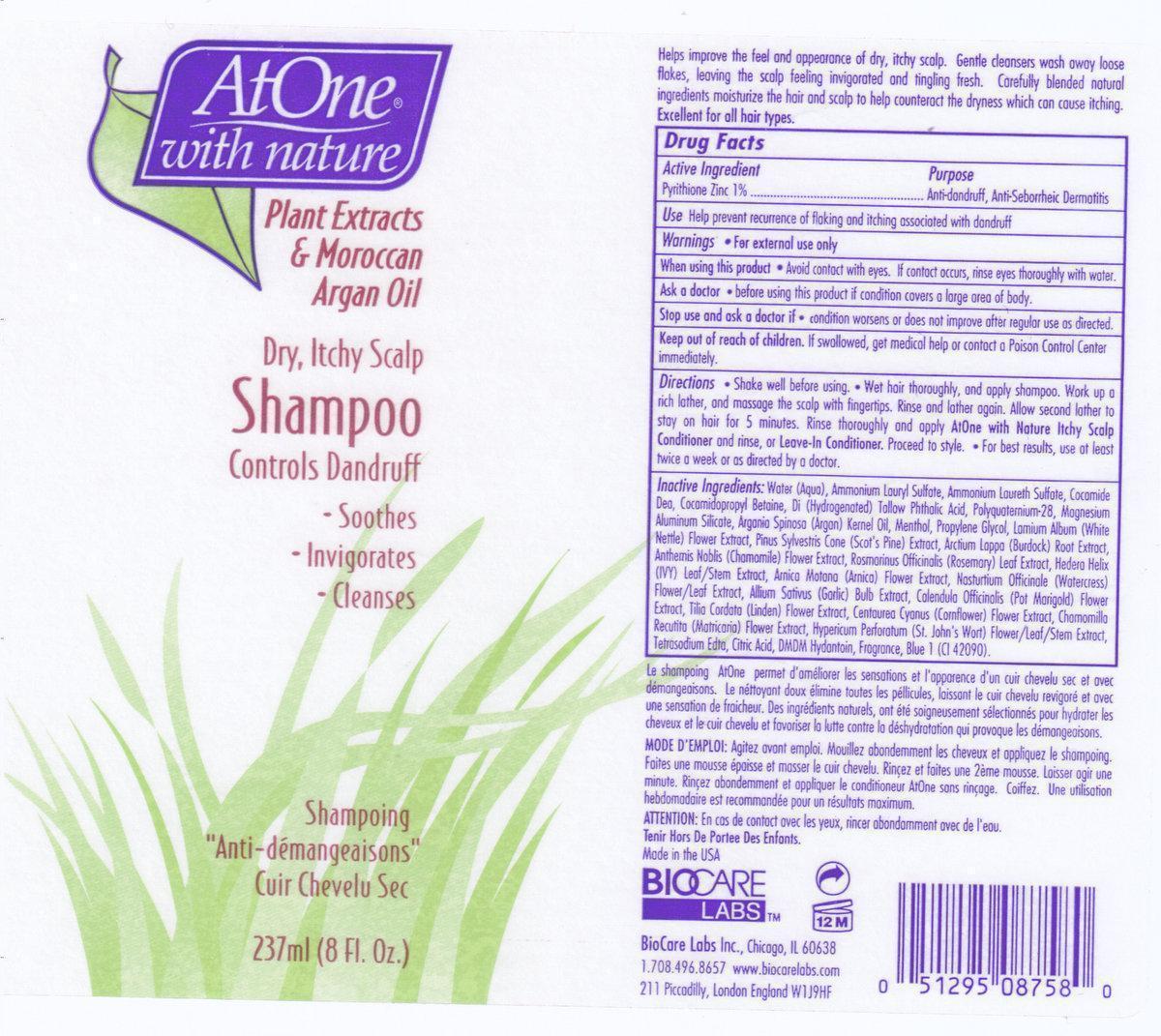 DRUG LABEL: AT ONE WITH NATURE
NDC: 54602-758 | Form: SHAMPOO
Manufacturer: BIOCARE LABS INC.
Category: otc | Type: HUMAN OTC DRUG LABEL
Date: 20121227

ACTIVE INGREDIENTS: PYRITHIONE ZINC 10 mg/1 mL
INACTIVE INGREDIENTS: WATER; AMMONIUM LAURETH-2 SULFATE; AMMONIUM LAURYL SULFATE; COCO DIETHANOLAMIDE; DIHYDROGENATED TALLOW PHTHALIC ACID AMIDE; COCAMIDOPROPYL BETAINE; GLYCOL STEARATE; MENTHOL; MAGNESIUM ALUMINUM SILICATE; PROPYLENE GLYCOL; LAMIUM ALBUM; PINE NEEDLE OIL (PINUS SYLVESTRIS); POLYQUATERNIUM-28 (1100000 MW); ARGAN OIL; ARCTIUM LAPPA ROOT; ROSEMARY; HEDERA HELIX LEAF; ARNICA MONTANA FLOWER; NASTURTIUM OFFICINALE FLOWERING TOP; GARLIC; CALENDULA OFFICINALIS FLOWER; TILIA CORDATA FLOWER; CENTAUREA CYANUS FLOWER; CHAMAEMELUM NOBILE FLOWER; CHAMOMILE; HYPERICUM PERFORATUM; DMDM HYDANTOIN; CITRIC ACID MONOHYDRATE; EDETATE SODIUM; FD&C BLUE NO. 1

Active Ingredients:

Pyrithione Zinc 1%

Purpose: Antidandruff, Anti-Seborrheic Dermatitis

INDICATIONS AND USAGE

Use: Help prevent recurrence of flaking and itching associated with dandruff.

Warnings:

- For external use only.

When using this product

- Avoid getting into eyes. In event of contact, rinse eyes thoroughly with water.

Ask a doctor. before using this product if condition covers a large area of body.

Stop use and ask a doctor if. conditions worsens or does not improve after regular use as directed.

Keep out of reach of children.If swallowed, get medical help or contact a Poison Control Center immediately.

Directions

- Shake before using.
- Wet hair thoroughly, and apply shampoo.Work up a rich lather, and massage the scalp with fingertips. Rinse and lather again.Allow second lather to stay on hair for 5 minutes.Rinse thoroughly and apply AtOne with Nature Itchy Scalp Conditioner and rinse, or Leave-In Conditioner.Proceed to style.
- For best results, use at least twice a week or as directed by a doctor.

Inactive Ingredients

Water(Aqua), Ammonium Laureth Sulfate, Ammonium Lauryl Sulfate, Cocamide DEA, Polyquaternium-28, Cocamidopropyl Betaine,Menthol,Glycol Stearate, Magnesium Aluminum Silicate, Dihydrogenated Tallow Phthalic Acid, Propylene Glycol, Lamium Album Flower Extract, Pinus Sylvestris Cone Extract, Arctium Lappa(Burdock) Root Extract, Anthemis Nobilis(Chamomile) Flower Extract, Rosmarinus Officinalis (Rosemary) Leaf Extract, Hedra Helix (Ivy) Leaf/Stem Extract, Arnica Montana Flower Extract, Nasturtium Officinale (Watercress) Flower/Leaf Extract, Allium Sativum (Garlic) Bulb Extract, Calendula Officinalis (Pot Marigold) Flower Extract, Tilia Cordata (Linden) Flower Extract, Centaurea Cyanus (Cornflower) Flower Extract, Chamomilla Recutita (Matricaria) Flower Extract, Hypericum Perfratum (St. John's Wort) Flower/Leaf/Stem Extract, Fragrance, DMDM Hydantion, Tetraodium EDTA, Citric Acid, Blue 1 (CI 42090) Argania spinosa (Argan) KERNEL Oil